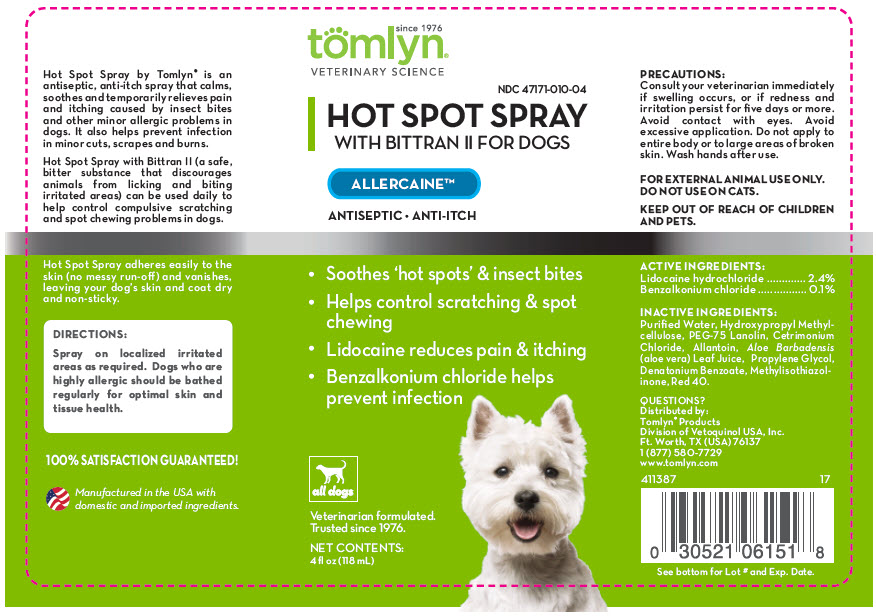 DRUG LABEL: Allercaine with Bittran II
NDC: 47171-010 | Form: SPRAY
Manufacturer: Tomlyn Products, a Division of Vetoquinol USA, Inc.
Category: animal | Type: OTC ANIMAL DRUG LABEL
Date: 20241217

ACTIVE INGREDIENTS: Lidocaine Hydrochloride 24 mg/1 mL; Benzalkonium Chloride 1 mg/1 mL
INACTIVE INGREDIENTS: Water; PEG-75 Lanolin; Aloe Vera Leaf; Hydroxymethyl Cellulose; Cetrimonium Bromide; Allantoin; Denatonium Benzoate

Allercaine™ with Bittran II™

VETERINARY INDICATIONS

Hot Spot Spray by Tomlyn® is an antiseptic, anti-itch spray that calms, soothes and temporarily relieves pain and itching caused by insect bites and other minor allergic problems in dogs. It also helps prevent infection in minor cuts, scrapes and burns.

Hot Spot Spray with Bittran™ II (a safe, bitter substance that discourages animals from licking and biting irritated areas) can be used daily to help control compulsive scratching and spot chewing problems in dogs. Hot Spot Spray adheres easily to the skin (no messy run-off) and vanishes, leaving your dog's skin and coat dry and non-sticky.

DIRECTIONS:

Spray on localized irritated areas as required. Dogs who are highly allergic should be bathed regularly for optimal skin and tissue health.

PRECAUTIONS:

Consult your veterinarian immediately if swelling occurs, or if redness and irritation persist for five days or more. Avoid contact with eyes. Avoid excessive application. Do not apply to entire body or to large areas of broken skin. Wash hands after use.

FOR EXTERNAL ANIMAL USE ONLY.

DO NOT USE ON CATS.

KEEP OUT OF REACH OF CHILDREN AND PETS.

ACTIVE INGREDIENTS:

Lidocaine hydrochloride | 2.4%
Benzalkonium chloride | 0.1%

Compounded in a vanishing liquid base containing PEG-75 lanolin, aloe vera gel, allantoin and denatonium benzoate (Bittran™ II), among other ingredients. Stabilized at a pH of normal animal skin.

QUESTIONS?

Manufactured for:
Tomlyn® Products
Division of Vetoquinol USA, Inc.
Ft. Worth, TX (USA) 76137
1 (877) 580-7729
www.tomlyn.com

411388
14

100%
SATISFACTION
GUARANTEED!

Manufactured in the USA with
domestic and imported ingredients

Lot No:
Exp. Date

Learn more about the
story of Tom & Lyn at:
www.tomlyn.com

Promote healing and deter chewing of
wounds with Hot Spot Spray for dogs.
- Tom & Lyn

PRINCIPAL DISPLAY PANEL - 118 mL Bottle Label

since 1976
tomlyn®
VETERINARY SCIENCE

NDC 47171-010-04

HOT SPOT SPRAY
WITH BITTRAN II FOR DOGS

ALLERCAINE™

ANTISEPTIC • ANTI-ITCH

- Soothes 'hot spots' & insect bites
- Helps control scratching & spot
  chewing
- Lidocaine reduces pain & itching
- Benzalkonium chloride helps
  prevent infection

all dogs

Veterinarian formulated.
Trusted since 1976.

NET CONTENTS:
4 fl oz (118 mL)